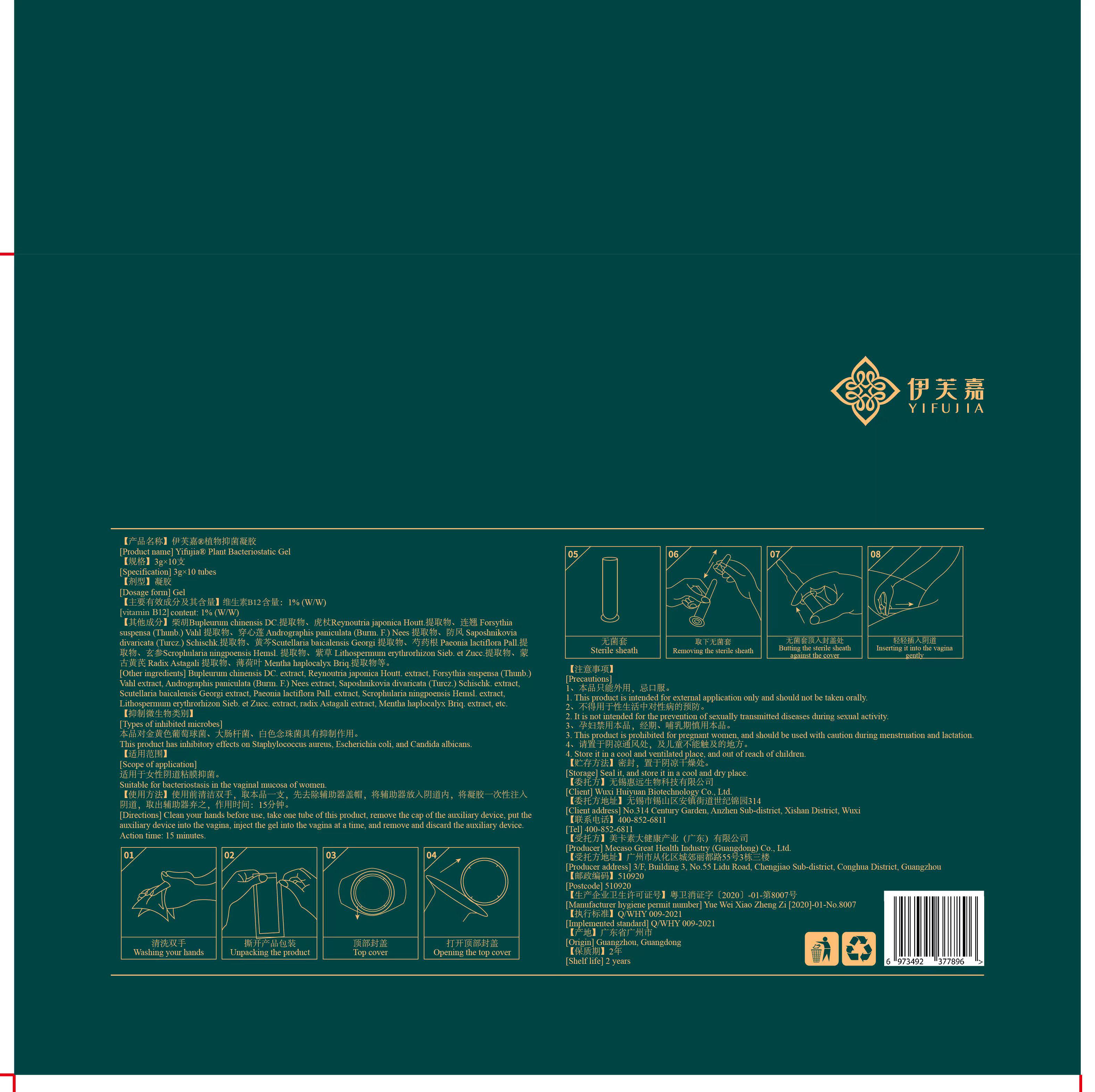 DRUG LABEL: YIFUJIA PLANT ANTIBACTERIAL Gel
NDC: 84341-002 | Form: GEL
Manufacturer: Mecaso Great Health Industry (Guangdong) Co.,Ltd.
Category: otc | Type: HUMAN OTC DRUG LABEL
Date: 20240521

ACTIVE INGREDIENTS: CYANOCOBALAMIN 1 g/100 g
INACTIVE INGREDIENTS: SAPOSHNIKOVIA DIVARICATA ROOT; SCROPHULARIA NINGPOENSIS ROOT; MENTHA CANADENSIS WHOLE; FORSYTHIA SUSPENSA FRUIT; ANDROGRAPHIS PANICULATA WHOLE; LITHOSPERMUM ERYTHRORHIZON ROOT; PAEONIA LACTIFLORA ROOT; ASTRAGALUS MONGHOLICUS ROOT; WATER; SCUTELLARIA BAICALENSIS ROOT; REYNOUTRIA JAPONICA WHOLE; SOPHORA FLAVESCENS ROOT; BUPLEURUM CHINENSE ROOT

YIFUJIA PLANT ANTIBACTERIAL GEL

ACTIVE INGREDIENT

vitamin B12 1%

PURPOSE

This product has inhibitory effects on Staphylococcus aureus, Escherichia coli. and Candida albicans

KEEP OUT OF REACH OF CHILDREN SECTION

INDICATIONS AND USAGE

Suitable for bacteriostasis in the vaginal mucosa of women

WARNINGS

This product is intended for external application only and should not be taken orally.
It is not intended for the prevention of sexually transmitted diseases during sexual activity.
This product is prohibited for pregnant women, and should be used with caution during menstruation and lactation.
Store it in a cool and ventilated place, and out of reach of children.

DOSAGE AND ADMINISTRATION

Clean your hands before use, take one tube of this product, remove the cap of the auxiliary device, put the auxilary device into the vagina, nect the gel into the vagina at a time. and remove and discard the auxiliary device.
Action time: 15 minutes

STORAGE AND HANDLING

Seal it, and store it in a cool and dry place

INACTIVE INGREDIENT

SOPHORA FLAVESCENS EXTRACT
BUPLEURUM CHINENSE EXTRACT
Reynoutria japonica Houtt. EXTRACT
FORSYTHIA SUSPENSA EXTRACT
ANDROGRAPHIS PANICULATA EXTRACT
SAPOSHNIKOVIA DIVARICATA EXTRACT
PAEONIA ALBIFLORA ROOT EXTRACT
SCUTELLARIA BAICALENSIS EXTRACT
SCROPHULARIA NINGPOENSIS EXTRACT
LITHOSPERMUM ERYTHRORHIZON EXTRACT
ASTRAGALUS MEMBRANACEUS MONGHOLICUS EXTRACT
MENTHA HAPLOCALYX LEAF EXTRACT
WATER